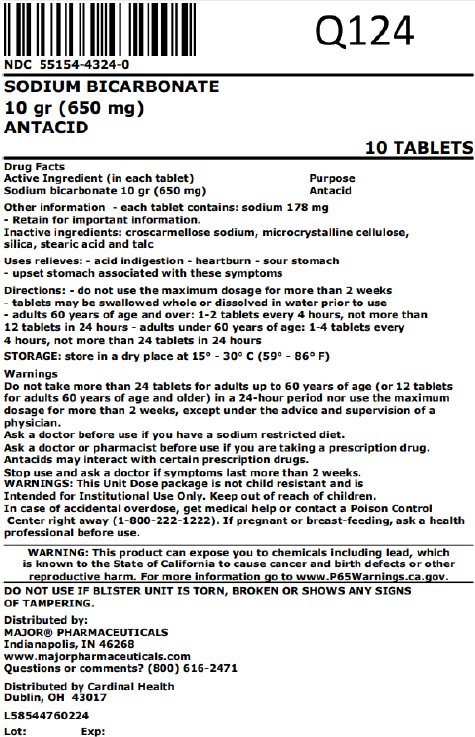 DRUG LABEL: Sodium Bicarbonate
NDC: 55154-4324 | Form: TABLET
Manufacturer: Cardinal Health 107, LLC
Category: otc | Type: HUMAN OTC DRUG LABEL
Date: 20251029

ACTIVE INGREDIENTS: SODIUM BICARBONATE 650 mg/1 1
INACTIVE INGREDIENTS: CROSCARMELLOSE SODIUM; MICROCRYSTALLINE CELLULOSE; SILICON DIOXIDE; STEARIC ACID; TALC

Sodium Bicarbonate

Drug Facts

Active ingredient (in each tablet)

Sodium bicarbonate 10 gr (650 mg)

Purpose

Antacid

Uses

relieves:

 acid indigestion

 heartburn

 sour stomach
 upset stomach associated with these symptoms

Warnings

DO NOT USE

Do not take more than 24 tablets for adults up to 60 years of age (or 12 tablets for
adults 60 years of age and older) in a 24-hour period nor use the maximum dosage
for more than 2 weeks, except under the advice and supervision of a physician.

Ask a doctor before use if you have a sodium restricted diet.

Ask a doctor or pharmacist before use if you are taking a prescription drug.
Antacids may interact with certain prescription drugs.

Stop use and ask a doctor if symptoms last more than 2 weeks.

PREGNANCY OR BREAST FEEDING

If pregnant or breast-feeding, ask a health professional before use.

Keep out of reach of children.

OVERDOSAGE

In case of accidental overdose, get medical help or contact a Poison Control Center right away (1-800-222-1222).

Directions

 do not use the maximum dosage for more than 2 weeks  tablets may be
swallowed whole or dissolved in water prior to use  adults 60 years of age
and over: 1-2 tablets every 4 hours, not more than 12 tablets in 24 hours
 adults under 60 years of age: 1-4 tablets every 4 hours, not more than 24
tablets in 24 hours

Other information

 each tablet contains: sodium 178 mg
 store in a dry place at 15° – 30°C (59° – 86°F)  Retain this carton for
important information.

Inactive Ingredients

croscarmellose sodium, microcrystalline cellulose, silica, stearic acid and talc

Questions or comments?

(800) 616-2471

Unit Dose

Sodium Bicarbonate

DO NOT USE IF CARTON IS OPENED OR IF A BLISTER UNIT IS TORN, BROKEN, OR SHOWS ANY SIGNS OF TAMPERING.

Distributed by:
MAJOR® PHARMACEUTICALS
Indianapolis, IN 46268
www.majorpharmaceuticals.com

WARNING: This product can expose you to chemicals including
lead, which is known to the State of California to cause cancer
and birth defects or other reproductive harm. For more information
go to www.P65Warnings.ca.gov.

Overbagged with 10 tablets per bag, NDC 55154-4324-0

WARNING: This Unit Dose package is not child resistant and is Intended for Institutional Use Only. Keep this and all drugs out of the reach of children.

Distributed By:

Cardinal Health

Dublin, OH 43017

L58544760224

Rev. 05/22 | M-29 | Re-order No. 701316

Principal Display Panel

NDC 55154-4324-0

SODIUM BICARBONATE

10 gr (650 mg)

ANTACID

10 TABLETS